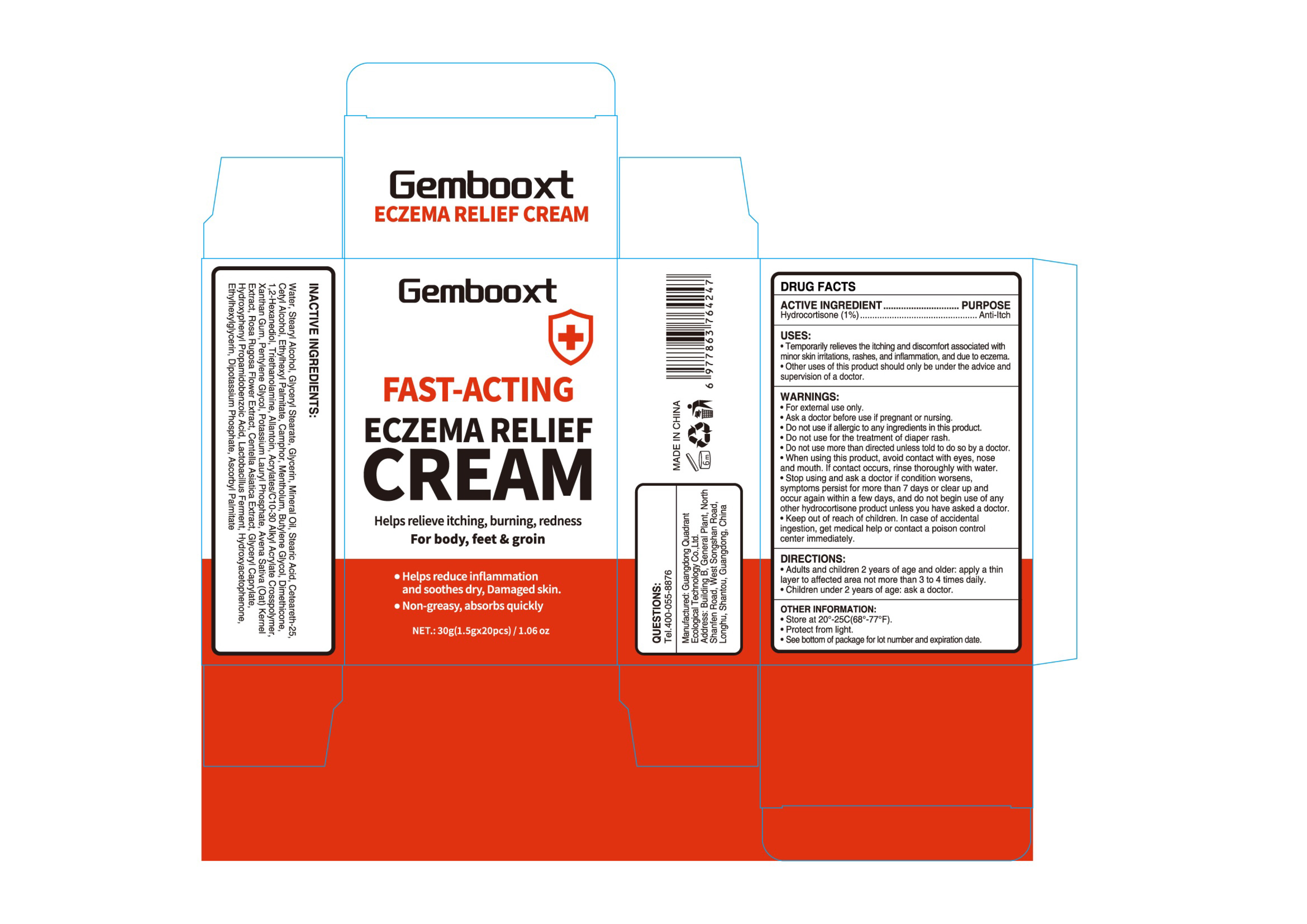 DRUG LABEL: Gembooxt ECZEMA RELIEF Cream
NDC: 76986-019 | Form: CREAM
Manufacturer: Guangdong Quadrant Ecological Technology Co., Ltd.
Category: otc | Type: HUMAN OTC DRUG LABEL
Date: 20251219

ACTIVE INGREDIENTS: HYDROCORTISONE 0.01 g/1 g
INACTIVE INGREDIENTS: WATER; CETEARETH-25; DIMETHICONE; DIBASIC POTASSIUM PHOSPHATE; HYDROXYPHENYL PROPAMIDOBENZOIC ACID; BUTYLENE GLYCOL; STEARYL ALCOHOL; XANTHAN GUM; STEARIC ACID; CAMPHOR (SYNTHETIC); ROSA RUGOSA FLOWER; ASCORBYL PALMITATE; POTASSIUM LAURYL PHOSPHATE; TRIETHANOLAMINE; CETYL ALCOHOL; ALLANTOIN; OAT; GLYCERYL CAPRYLATE; 1,2-HEXANEDIOL; ETHYLHEXYL PALMITATE; MINERAL OIL; MENTHOL; CENTELLA ASIATICA TRITERPENOIDS; HYDROXYACETOPHENONE; PENTYLENE GLYCOL; GLYCERYL STEARATE; ACRYLATES/C10-30 ALKYL ACRYLATE CROSSPOLYMER (60000 MPA.S AT 0.5%); GLYCERIN; LACTOBACILLUS REUTERI F275 STRAIN; ETHYLHEXYLGLYCERIN

76986-019 Gembooxt ECZEMA RELIEF CREAM

ACTIVE INGREDIENT

Hydrocortisone (1%)

PURPOSE

Anti-ltch

INDICATIONS AND USAGE

Temporarily relieves the itching and discomfort associated with minor skin irritations, rashes, and inflammation, and due to eczema.
Other uses of this product should only be under the advice and supervision of a doctor.

WARNINGS

For external use only.

Do not use if allergic to any ingredients in this product.
Do not use for the treatment of diaper rash.
Do not use more than directed unless told to do so by a doctor.

When using this product, avoid contact with eyes, nose and mouth. lf contact occurs, rinse thoroughly with water.

Ask a doctor before use if pregnant or nursing

STOP USE

Stop using and ask a doctor if condition worsens,symptoms persist for more than 7 days or clear up and occur again within a few days, and do not begin use of any other hydrocortisone product unless you have asked a doctor.

Keep out of reach of children. In case of accidental ingestion, get medical help or contact a poison control center immediately.

DOSAGE AND ADMINISTRATION

Adults and children 2 years of age and older: apply a thin layer to affected area not more than 3 to 4 times daily.

Children under 2 years of age: ask a doctor.

INACTIVE INGREDIENT

WATER
CETYL ALCOHOL
STEARYL ALCOHOL
GLYCERYL STEARATE
GLYCERIN
MINERAL OIL
CETEARETH-25
STEARIC ACID
ETHYLHEXYL PALMITATE
CAMPHOR
MENTHOLUM
CENTELLA ASIATICA EXTRACT
AVENA SATIVA (OAT) KERNEL EXTRACT
ROSA RUGOSA FLOWER EXTRACT
LACTOBACILLUS FERMENT
BUTYLENE GLYCOL
DIMETHICONE
GLYCERYL CAPRYLATE
HYDROXYACETOPHENONE
ETHYLHEXYLGLYCERIN
1,2-HEXANEDIOL
TRIETHANOLAMINE
ALLANTOIN
ACRYLATES/C10-30 ALKYL ACRYLATE CROSSPOLYMER
XANTHAN GUM
BUTYLENE GLYCOL
PENTYLENE GLYCOL
HYDROXYPHENYL PROPAMIDOBENZOIC ACID
ASCORBYL PALMITATE
POTASSIUM LAURYL PHOSPHATE
DIPOTASSIUM PHOSPHATE